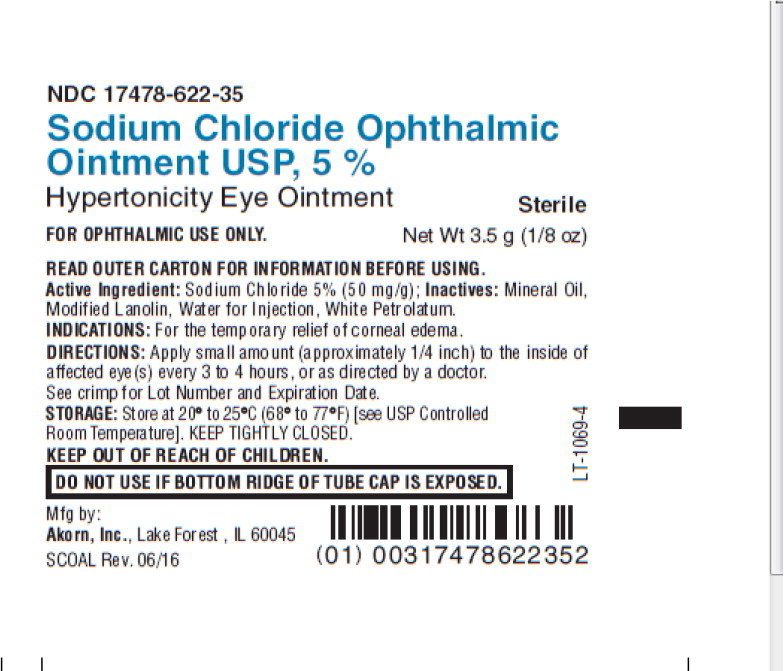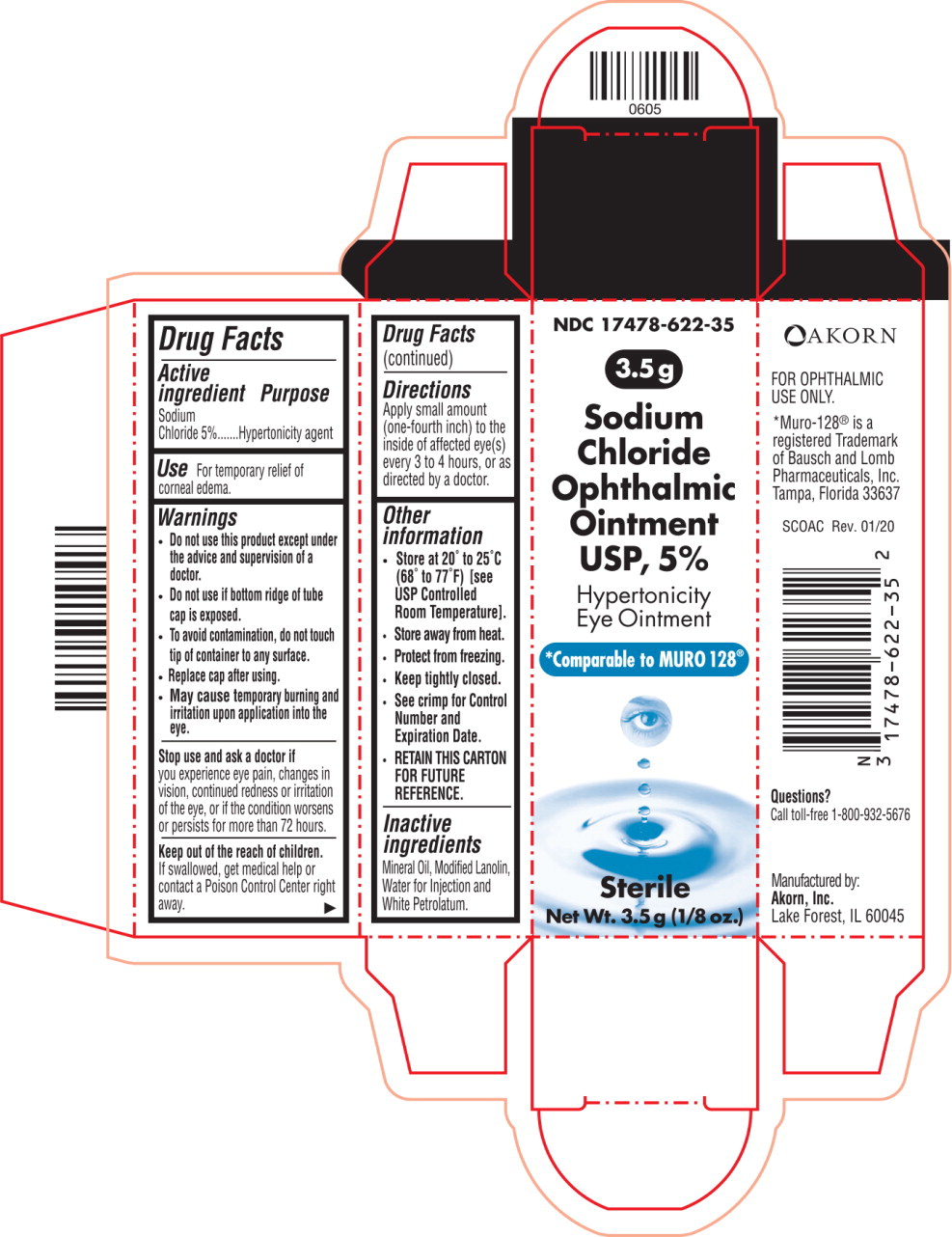 DRUG LABEL: Sodium Chloride
NDC: 17478-622 | Form: OINTMENT
Manufacturer: Akorn
Category: otc | Type: HUMAN OTC DRUG LABEL
Date: 20220207

ACTIVE INGREDIENTS: Sodium Chloride 50 mg/1 g
INACTIVE INGREDIENTS: Mineral Oil; Lanolin; Water; Petrolatum

Drug Facts

Active ingredient

Sodium Chloride 5%

Purpose

Hypertonicity agent

Use

for temporary relief of corneal edema.

Warnings

- Do not use this product except under the advice and supervision of a doctor.
- Do not use if bottom ridge of tube cap is exposed
- To avoid contamination, do not touch tip of container to any surface.
- Replace cap after using.
- May cause temporary burning and irritation upon application into the eye.

Stop use and ask a doctor if

you experience eye pain, changes in vision, continued redness or irritation of the eye, or if the condition worsens or persists for more than 72 hours.

Keep out of reach of children.

If swallowed, get medical help or contact a Poison Control Center right away.

Directions

Apply small amount (one-fourth inch) to the inside of affected eye(s) every 3 to 4 hours, or as directed by a doctor.

Other information

- Store at 20° to 25°C (68° to 77°F) [see USP Controlled Room Temperature].
- Store away from heat.
- Protect from freezing.
- Keep tightly closed.
- See crimp for Control Number and Expiration Date.
- RETAIN THIS CARTON FOR FUTURE REFERENCE.

Inactive ingredients

Mineral Oil, Modified Lanolin, Water for Injection and White Petrolatum.

Principal Display Panel Text for Container Label:

NDC 17478-622-35

Sodium Chloride Ophthalmic

Ointment USP, 5%

Hypertonicity Eye Ointment Sterile

FOR OPHTHALMIC USE ONLY. Net Wt. 3.5 g (1/8 oz.)

Principal Display Panel Text for Carton Label:

NDC 17478-622-35

3.5 g

Sodium

Chloride

Ophthalmic

Ointment

USP, 5%

Hypertonicity

Eye Ointment

Comparable to MURO 128®

Sterile

Net Wt. 3.5 g (1/8 oz.)